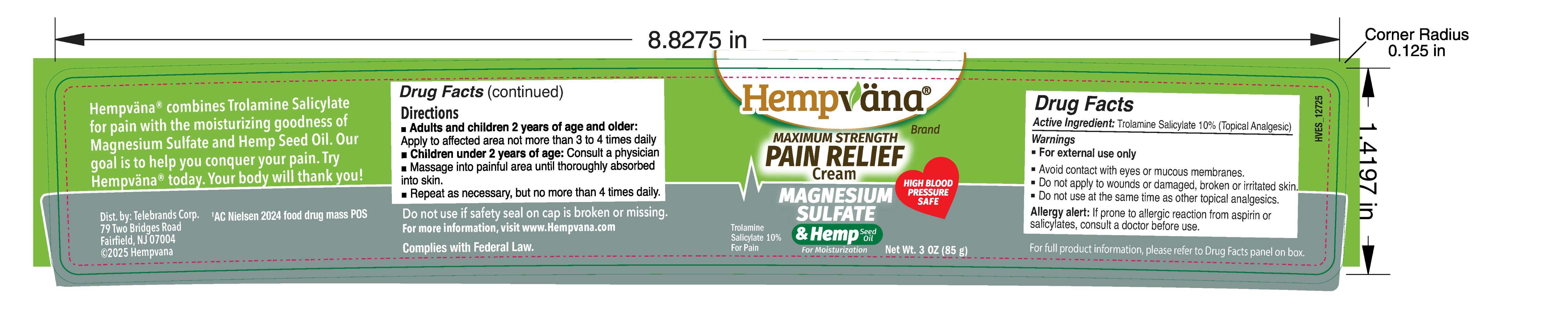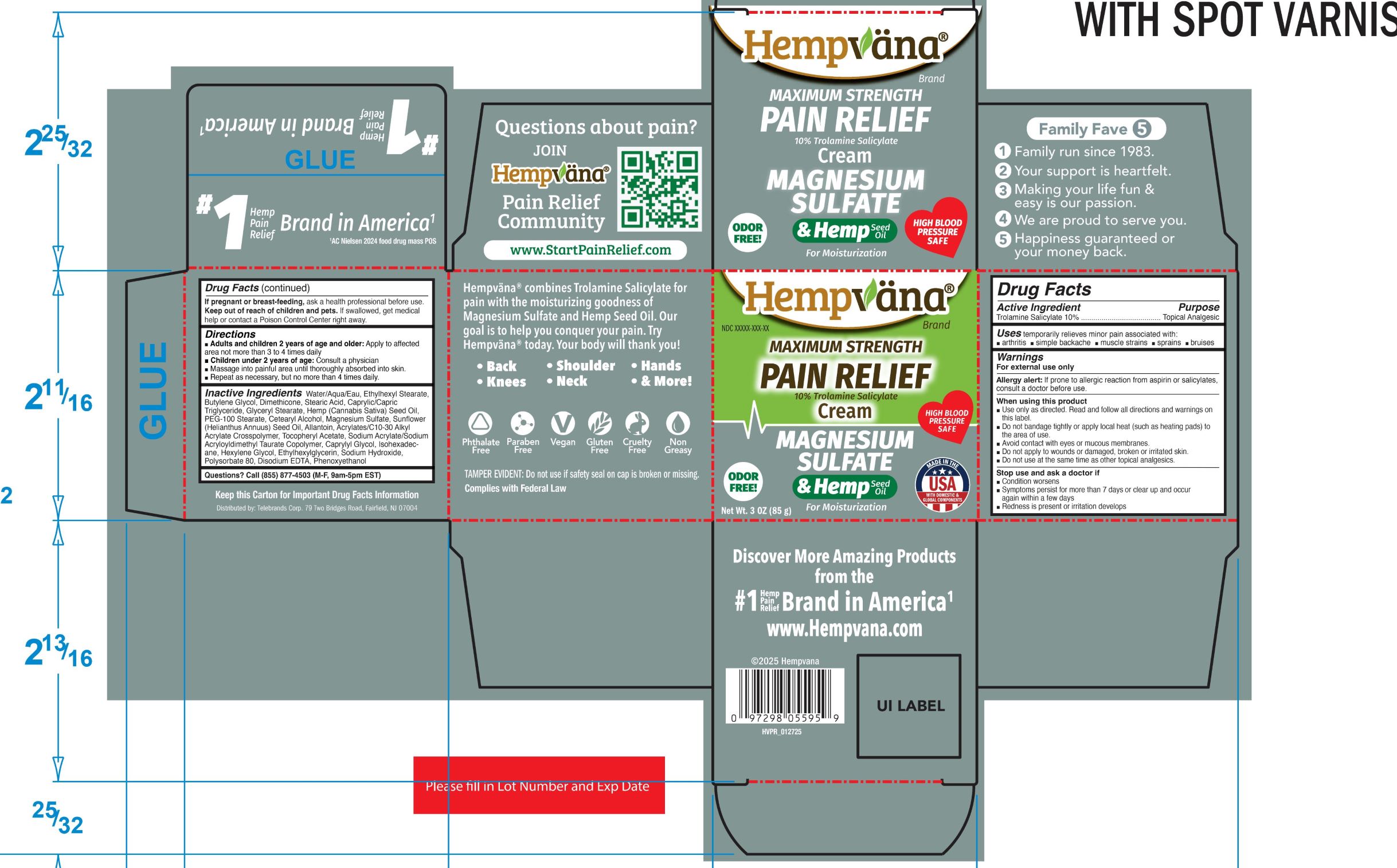 DRUG LABEL: Hempvana Maximum Strength Pain Relief Cream 10% Trolamine Salicylate
NDC: 73287-034 | Form: CREAM
Manufacturer: TELEBRANDS CORP
Category: otc | Type: HUMAN OTC DRUG LABEL
Date: 20250401

ACTIVE INGREDIENTS: TROLAMINE SALICYLATE 10 g/100 g
INACTIVE INGREDIENTS: MAGNESIUM SULFATE; SODIUM ACRYLATE/SODIUM ACRYLOYLDIMETHYLTAURATE COPOLYMER (4000000 MW); CAPRYLYL GLYCOL; POLYSORBATE 80; ETHYLHEXYL STEARATE; SODIUM HYDROXIDE; SUNFLOWER OIL; WATER; BUTYLENE GLYCOL; .ALPHA.-TOCOPHEROL ACETATE; PHENOXYETHANOL; ETHYLHEXYLGLYCERIN; EDETATE DISODIUM ANHYDROUS; PEG-100 STEARATE; STEARIC ACID; ALLANTOIN; HEXYLENE GLYCOL; DIMETHICONE; CANNABIS SATIVA SEED OIL; GLYCERYL MONOSTEARATE; ISOHEXADECANE; CAPRYLIC/CAPRIC TRIGLYCERIDE; CETEARYL ALCOHOL; ACRYLATES/C10-30 ALKYL ACRYLATE CROSSPOLYMER (60000 MPA.S AT 0.5%)

Hempvana Maximum Strength Pain Relief Cream 10% Trolamine Salicylate

Active Ingredient

Trolamine Salicylate 10%

Purpose

Trolamine Salicylate 10%..................Topical Analgesic

Uses

temporarily relieves minor pain associated with:

- arthritis
- simple backache
- muscle strains
- sprains
- bruises

Warnings

For external use only

Allergy alert:If prone to allergic reaction from aspirin or salicylates, consult a doctor before use.

When using this product

- Use only as directed. Read and follow all directions and warnings on this label.
- Do not bandage tightly or apply local heat (such as heating pads) to the area of use.
- Avoid contact with eyes or mucous membranes.
- Do not apply to wounds or damaged, broken, or irritated skin.
- Do not use at the same time as other topical analgesics.

Stop use and ask a doctor if

- Condition worsens
- Symptoms persist for more than 7 days or clear up and occur again within a few days
- Redness is present or irritation develops

PREGNANCY OR BREAST FEEDING

If pregnant or breast-feeding,ask a health professional before use.

Keep out of reach of children and pets.If swallowed, get medical help or contact a Poison Control Center right away.

Directions

- Adults and children 2 years of age and older:apply to affected area not more than 3 to 4 times daily using roller ball applicator
- Children under 2 years of age:consult a physician

Inactive Ingredients

Water/Aqua/Eau, Ethylhexyl Stearate,Butylene Glycol, Dimethicone, Stearic Acid, Caprylic/CapricTriglyceride, Glyceryl Stearate, Hemp (Cannabis Sativa) Seed Oil,PEG-100 Stearate, Cetearyl Alcohol, Magnesium Sulfate, Sunflower(Helianthus Annuus) Seed Oil, Allantoin, Acrylates/C10-30 AlkylAcrylate Crosspolymer, Tocopheryl Acetate, Sodium Acrylate/SodiumAcryloyldimethyl Taurate Copolymer, Caprylyl Glycol, Isohexadecane, Hexylene Glycol, Ethylhexylglycerin, Sodium Hydroxide,Polysorbate 80, Disodium EDTA, Phenoxyethanol

Questions?

Call (855) 877-4503 (M-F, 9am-5pm EST)

PACKAGE LABEL

Hempvana Brand

Maximum Strength Pain Relief Cream

10% Trolamine Salicylate

Magnesium Sulfate & Hemp Seed Oil for moisturization

Net Wt. 3 OZ (85 g)